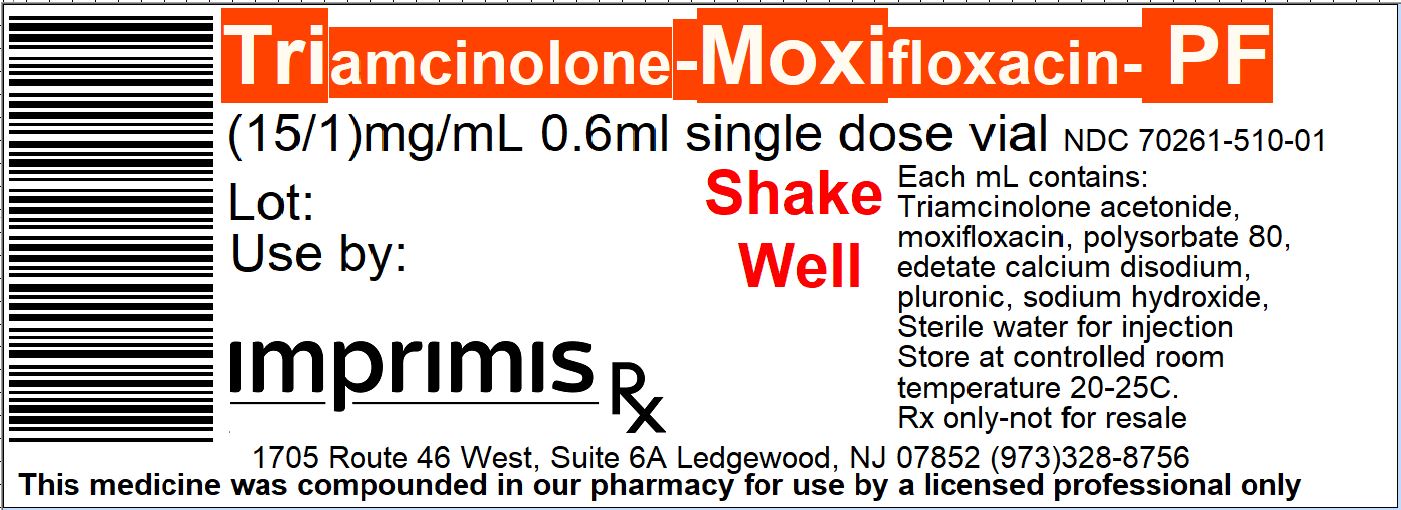 DRUG LABEL: Triamcinolone-Moxifloxacin PF
NDC: 70261-510 | Form: SUSPENSION
Manufacturer: ImprimisRx NJ
Category: prescription | Type: HUMAN PRESCRIPTION DRUG LABEL
Date: 20180227

ACTIVE INGREDIENTS: MOXIFLOXACIN HYDROCHLORIDE 1 mg/1 mL; TRIAMCINOLONE ACETONIDE 15 mg/1 mL

STORAGE AND HANDLING

Store at 20° to 25° C (68° to 77° F)